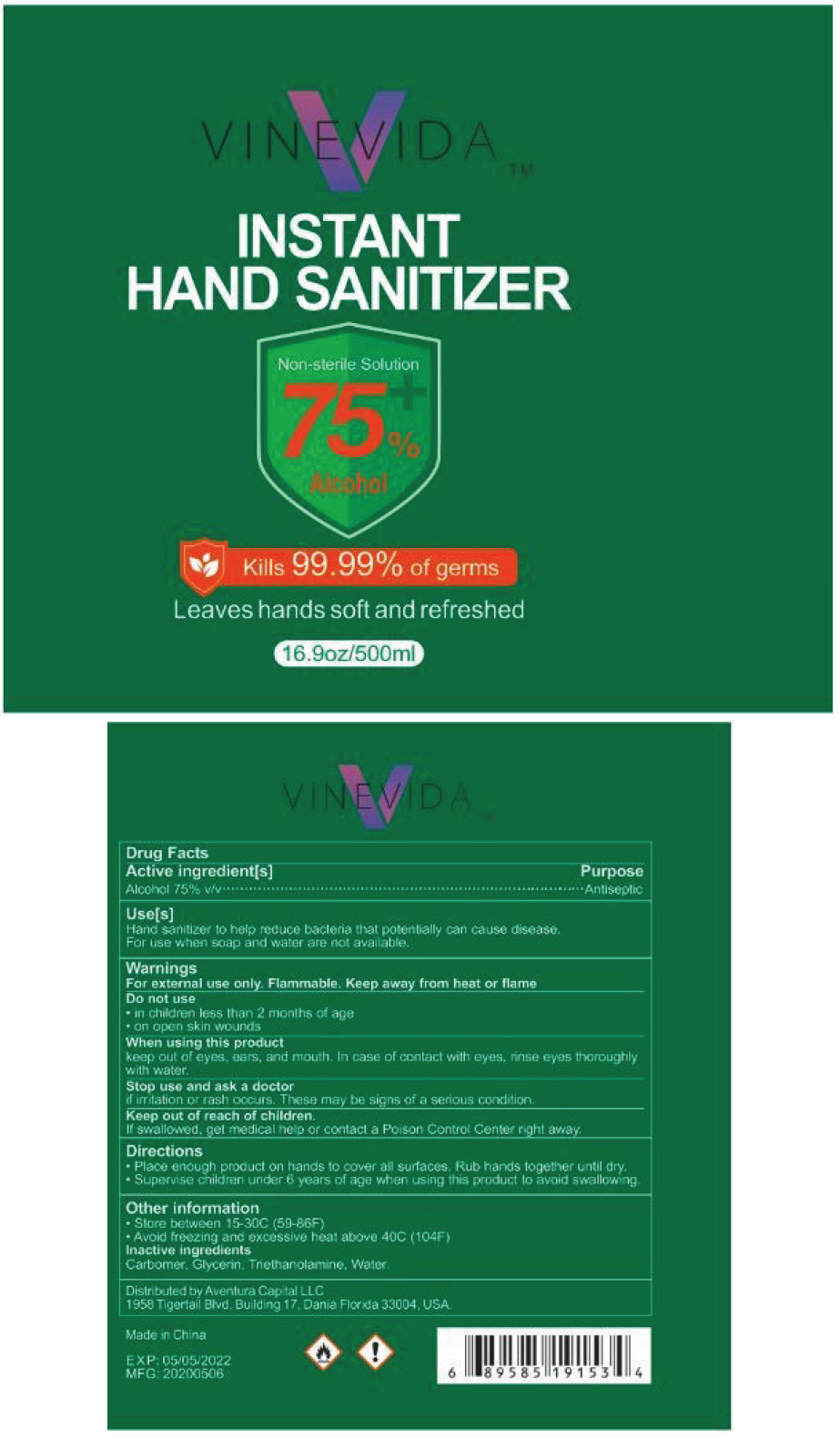 DRUG LABEL: VINEVIDA INSTANT HAND SANITIZER
NDC: 79430-002 | Form: GEL
Manufacturer: Aventura Capital LLC
Category: otc | Type: HUMAN OTC DRUG LABEL
Date: 20200716

ACTIVE INGREDIENTS: Alcohol 75 mL/100 mL
INACTIVE INGREDIENTS: CARBOMER HOMOPOLYMER, UNSPECIFIED TYPE; GLYCERIN; TROLAMINE; WATER

VINEVIDA™ INSTANT HAND SANITIZER

Drug Facts

Active ingredient[s]

Alcohol 75% v/v

Purpose

Antiseptic

Use[s]

Hand sanitizer to help reduce bacteria that potentially can cause disease.

For use when soap and water are not available.

Warnings

For external use only. Flammable. Keep away from heat or flame.

Do not use

- in children less than 2 months of age
- on open skin wounds

When using this product

keep out of eyes, ears, and mouth. In case of contact with eyes, rinse eyes thoroughly with water.

stop use and ask a doctor

if irritation or rash occurs. These may be signs of a serious condition.

Keep out of reach of children.

If swallowed, get medical help, or contact a Poison Control Center right away.

Directions

- Place enough product on hands to cover all surfaces. Rub hands together until dry.
- Supervise children under 6 years of age when using this product to avoid swallowing.

Other information

- Store between 15 – 30C (59-86F)
- Avoid freezing and excessive heat above 40C (104F)

Inactive ingredients

glycerin, hydrogen peroxide, purified water USP

Distributed by Aventura Capital LLC
1958 Tigertail Blvd, Building 17, Dania Beach 33004

PRINCIPAL DISPLAY PANEL - 500 ml Bottle Label

VINEVIDA™

INSTANT
HAND SANITIZER

Non-sterile Solution
75%
Alcohol

Kills 99.99% of germs

Leaves hands soft and refreshed

16.9oz/500ml